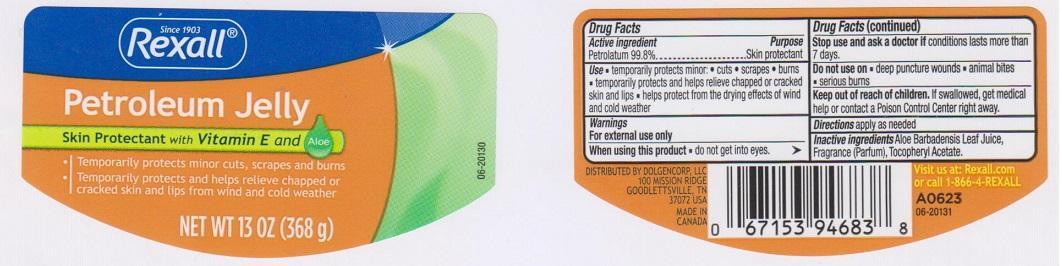 DRUG LABEL: REXALL
NDC: 55910-316 | Form: JELLY
Manufacturer: DOLGENCORP INC
Category: otc | Type: HUMAN OTC DRUG LABEL
Date: 20150304

ACTIVE INGREDIENTS: PETROLATUM 99.8 g/100 g
INACTIVE INGREDIENTS: ALOE VERA LEAF; .ALPHA.-TOCOPHEROL ACETATE

DRUG FACTS

ACTIVE INGREDIENT

PETROLATUM 99.8%

PURPOSE

SKIN PROTECTANT

USE

- TEMPORARILY PROTECTS MINOR:
- CUTS
- SCRAPES
- BURNS
- TEMPORARILY PROTECTS AND HELPS RELIEVE CHAPPED OR CRACKED SKIN AND LIPS
- HELPS PROTECT FROM THE DRYING EFFECTS OF WIND AND COLD WEATHER

WARNINGS

FOR EXTERNAL USE ONLY

WHEN USING THIS PRODUCT

DO NOT GET INTO EYES

STOP USE AND ASK A DOCTOR IF

CONDITIONS LASTS MORE THAN 7 DAYS

DO NOT USE ON

- DEEP PUNCTURE WOUNDS
- ANIMAL BITES
- SERIOUS BURNS

KEEP OUT OF REACH OF CHIDREN

IF SWALLOWED, GET MEDICAL HELP OR CONTACT A POISON CONTROL CENTER RIGHT AWAY

DIRECTIONS

APPLY AS NEEDED

INACTIVE INGREDIENTS

ALOE BARBADENSIS LEAF JUICE, FRAGRANCE (PARFUM), TOCOPHERYL ACETATE